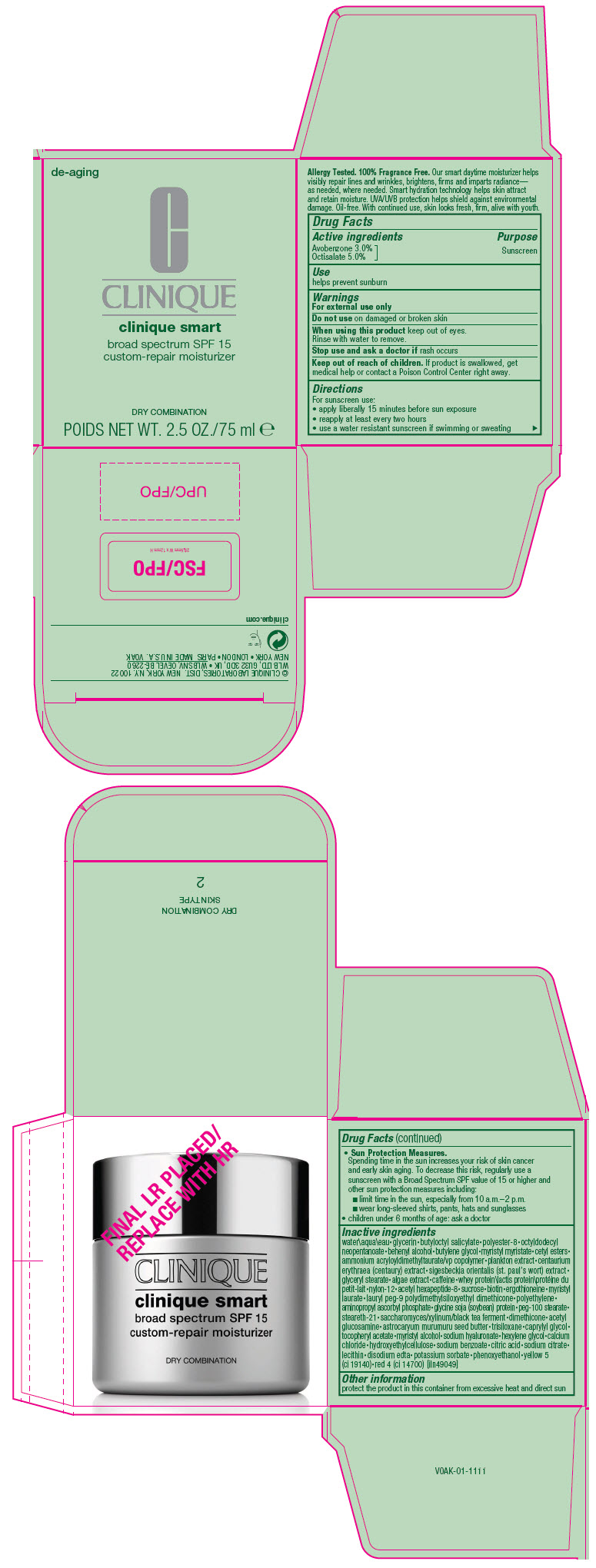 DRUG LABEL: CLINIQUE  SMART BROAD SPECTRUM SPF  15 CUSTOM-REPAIR MOISTURIZER DRY COMBINATION
NDC: 49527-051 | Form: CREAM
Manufacturer: CLINIQUE LABORATORIES LLC
Category: otc | Type: HUMAN OTC DRUG LABEL
Date: 20241225

ACTIVE INGREDIENTS: AVOBENZONE 30 mg/1 mL; OCTISALATE 50 mg/1 mL
INACTIVE INGREDIENTS: WATER; GLYCERIN; BUTYLOCTYL SALICYLATE; POLYESTER-8 (1400 MW, CYANODIPHENYLPROPENOYL CAPPED); OCTYLDODECYL NEOPENTANOATE; BUTYLENE GLYCOL; MYRISTYL MYRISTATE; CETYL ESTERS WAX; AMMONIUM ACRYLOYLDIMETHYLTAURATE/VP COPOLYMER; BLUEFISH; CENTAURIUM ERYTHRAEA; GLYCERYL MONOSTEARATE; CAFFEINE; NYLON-12; ACETYL HEXAPEPTIDE-8; SUCROSE; BIOTIN; ERGOTHIONEINE; MYRISTYL LAURATE; LAURYL PEG-9 POLYDIMETHYLSILOXYETHYL DIMETHICONE; HIGH DENSITY POLYETHYLENE; AMINOPROPYL ASCORBYL PHOSPHATE; SOYBEAN; PEG-100 STEARATE; STEARETH-21; DIMETHICONE; N-ACETYLGLUCOSAMINE; ASTROCARYUM MURUMURU SEED BUTTER; TRISILOXANE; CAPRYLYL GLYCOL; .ALPHA.-TOCOPHEROL ACETATE; MYRISTYL ALCOHOL; HYALURONATE SODIUM; HEXYLENE GLYCOL; SODIUM BENZOATE; SODIUM CITRATE, UNSPECIFIED FORM; EDETATE DISODIUM ANHYDROUS; PHENOXYETHANOL; FD&C YELLOW NO. 5; FD&C RED NO. 4; DOCOSANOL; SIGESBECKIA ORIENTALIS WHOLE; AGAR, UNSPECIFIED; WHEY PROTEIN HYDROLYSATE; SACCHAROMYCES CEREVISIAE; CALCIUM CHLORIDE; HYDROXYETHYL CELLULOSE, UNSPECIFIED; CITRIC ACID ACETATE; LECITHIN, SOYBEAN; POTASSIUM SORBATE

CLINIQUE SMART BROAD SPECTRUM SPF 15 CUSTOM-REPAIR MOISTURIZER DRY COMBINATION

Drug Facts

Active ingredients

Avobenzone 3.0%
Octisalate 5.0%

Purpose

Sunscreen

Use

helps prevent sunburn

Warnings

For external use only

Do not use on damaged or broken skin

When using this product keep out of eyes. Rinse with water to remove.

Stop use and ask a doctor if rash occurs

Keep out of reach of children. If product is swallowed, get medical help or contact a Poison Control Center right away.

Directions

For sunscreen use:

- apply liberally 15 minutes before sun exposure
- reapply at least every two hours
- use a water resistant sunscreen if swimming or sweating
- Sun Protection Measures.
  Spending time in the sun increases your risk of skin cancer and early skin aging. To decrease this risk, regularly use a sunscreen with a Broad Spectrum SPF value of 15 or higher and other sun protection measures including:
  - limit time in the sun, especially from 10 a.m.–2 p.m.
  - wear long-sleeved shirts, pants, hats and sunglasses
- children under 6 months of age: ask a doctor

Inactive ingredients

water\aqua\eau • glycerin • butyloctyl salicylate • polyester-8 • octyldodecyl neopentanoate • behenyl alcohol • butylene glycol • myristyl myristate • cetyl esters • ammonium acryloyldimethyltaurate/vp copolymer • plankton extract • centaurium erythraea (centaury) extract • sigesbeckia orientalis (st. paul's wort) extract • glyceryl stearate • algae extract • caffeine • whey protein\lactis protein\protéine du petit-lait • nylon-12 • acetyl hexapeptide-8 • sucrose • biotin • ergothioneine • myristyl laurate • lauryl peg-9 polydimethylsiloxyethyl dimethicone • polyethylene • aminopropyl ascorbyl phosphate • glycine soja (soybean) protein • peg-100 stearate • steareth-21 • saccharomyces/xylinum/black tea ferment • dimethicone • acetyl glucosamine • astrocaryum murumuru seed butter • trisiloxane • caprylyl glycol • tocopheryl acetate • myristyl alcohol • sodium hyaluronate • hexylene glycol • calcium chloride • hydroxyethylcellulose • sodium benzoate • citric acid • sodium citrate • lecithin • disodium edta • potassium sorbate • phenoxyethanol • yellow 5 (ci 19140) • red 4 (ci 14700) [iln49049]

Other information

protect the product in this container from excessive heat and direct sun

PRINCIPAL DISPLAY PANEL - 75 ml Jar Carton

de-aging

CLINIQUE
clinique smart
broad spectrum SPF 15
custom-repair moisturizer

DRY COMBINATION
POIDS NET WT. 2.5 OZ./75 ml ℮